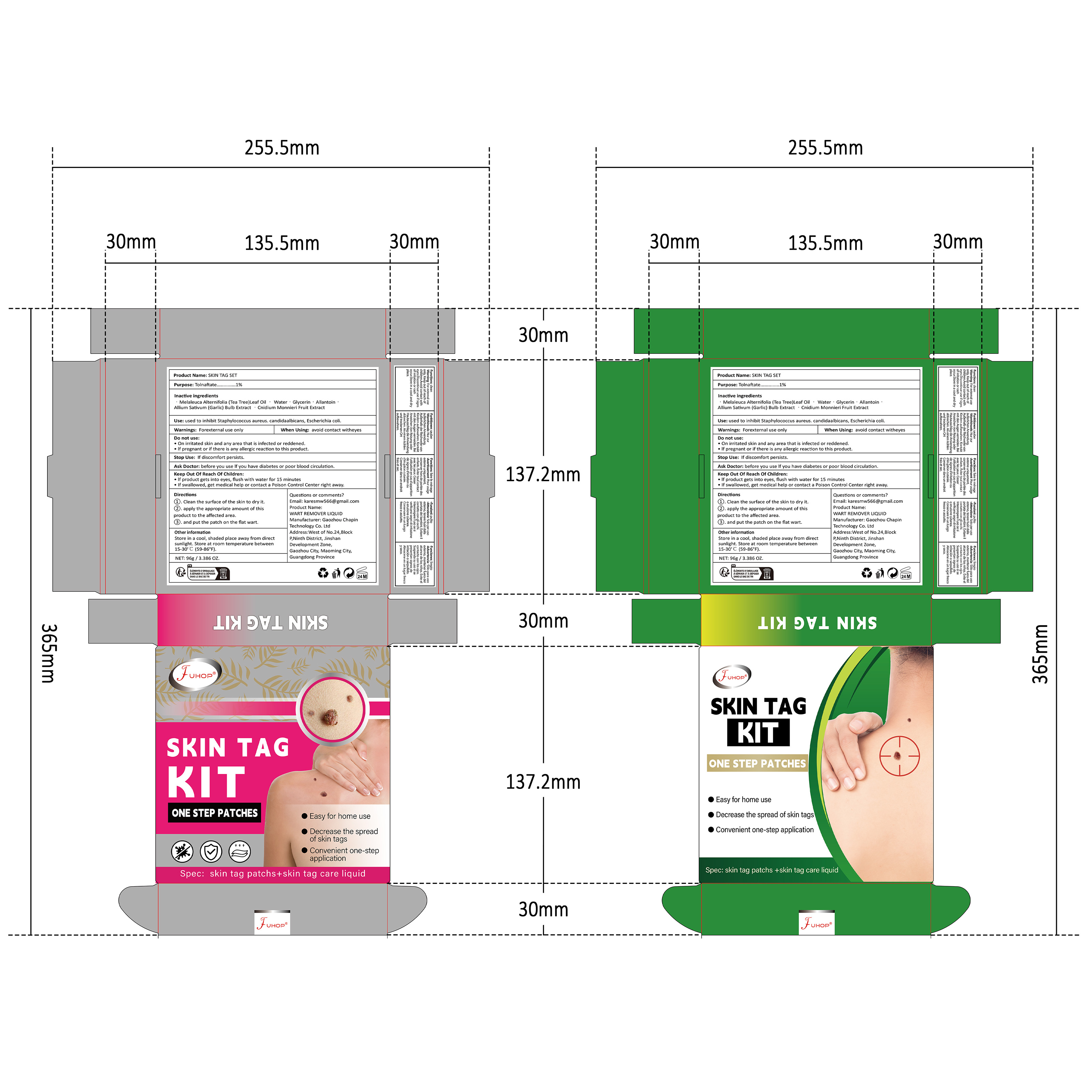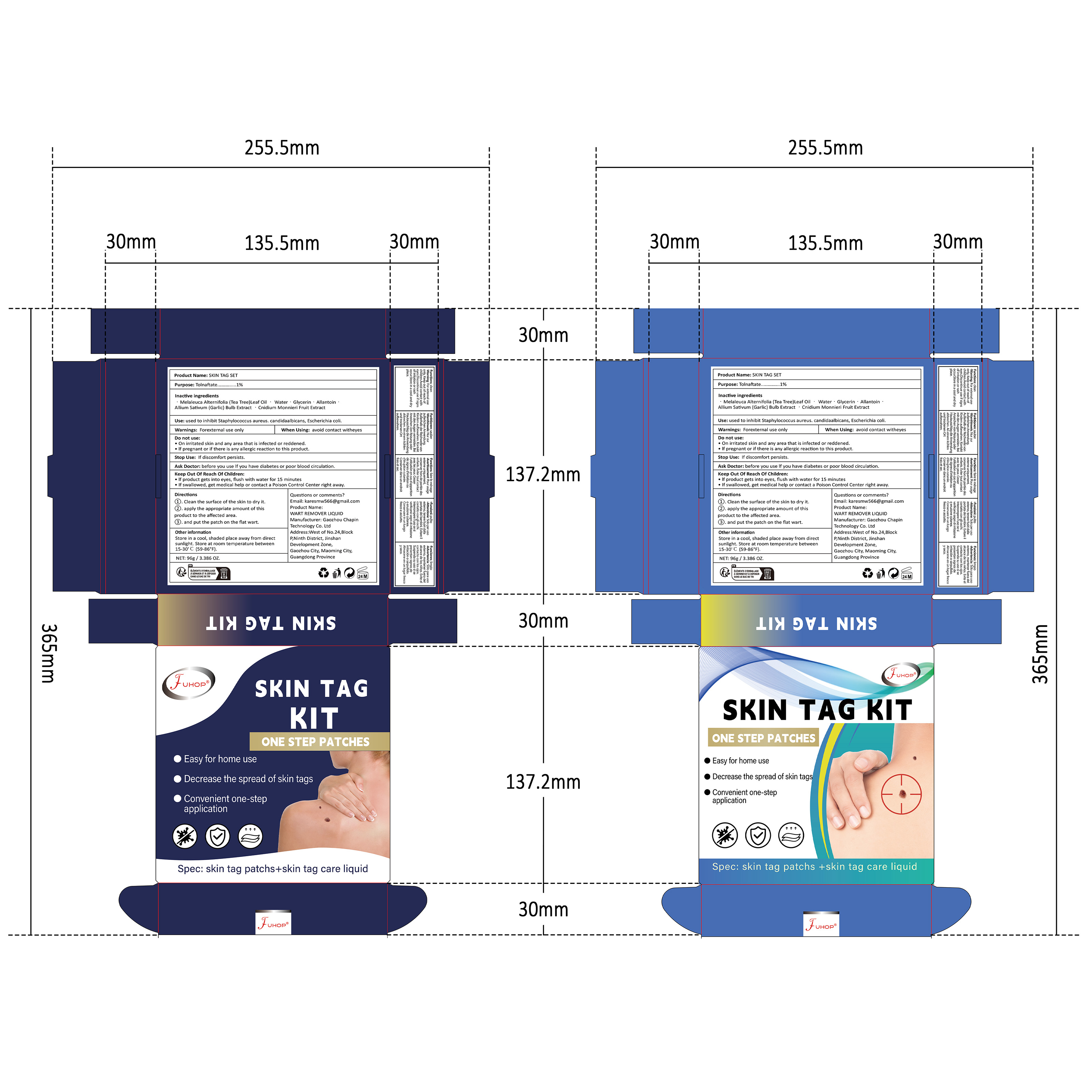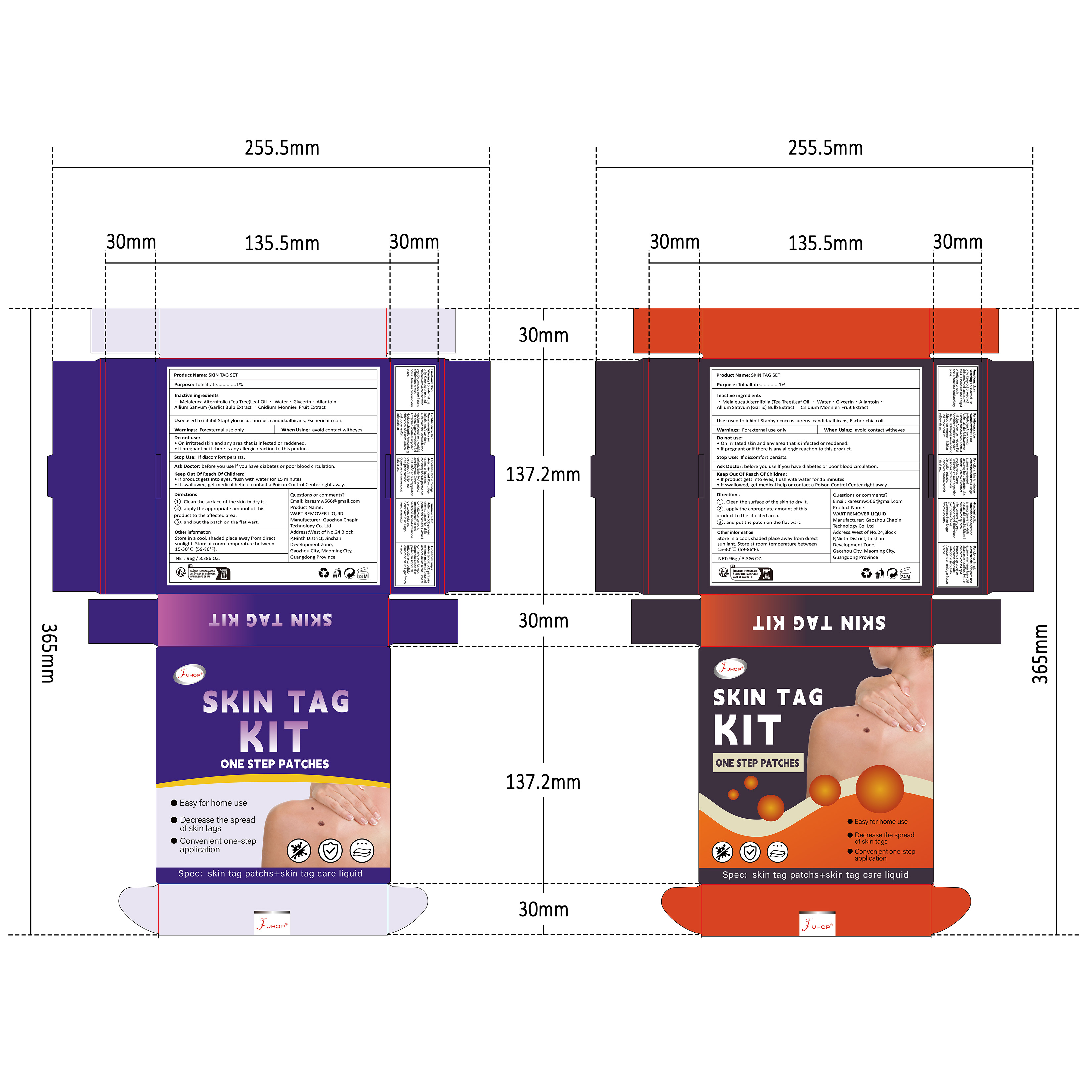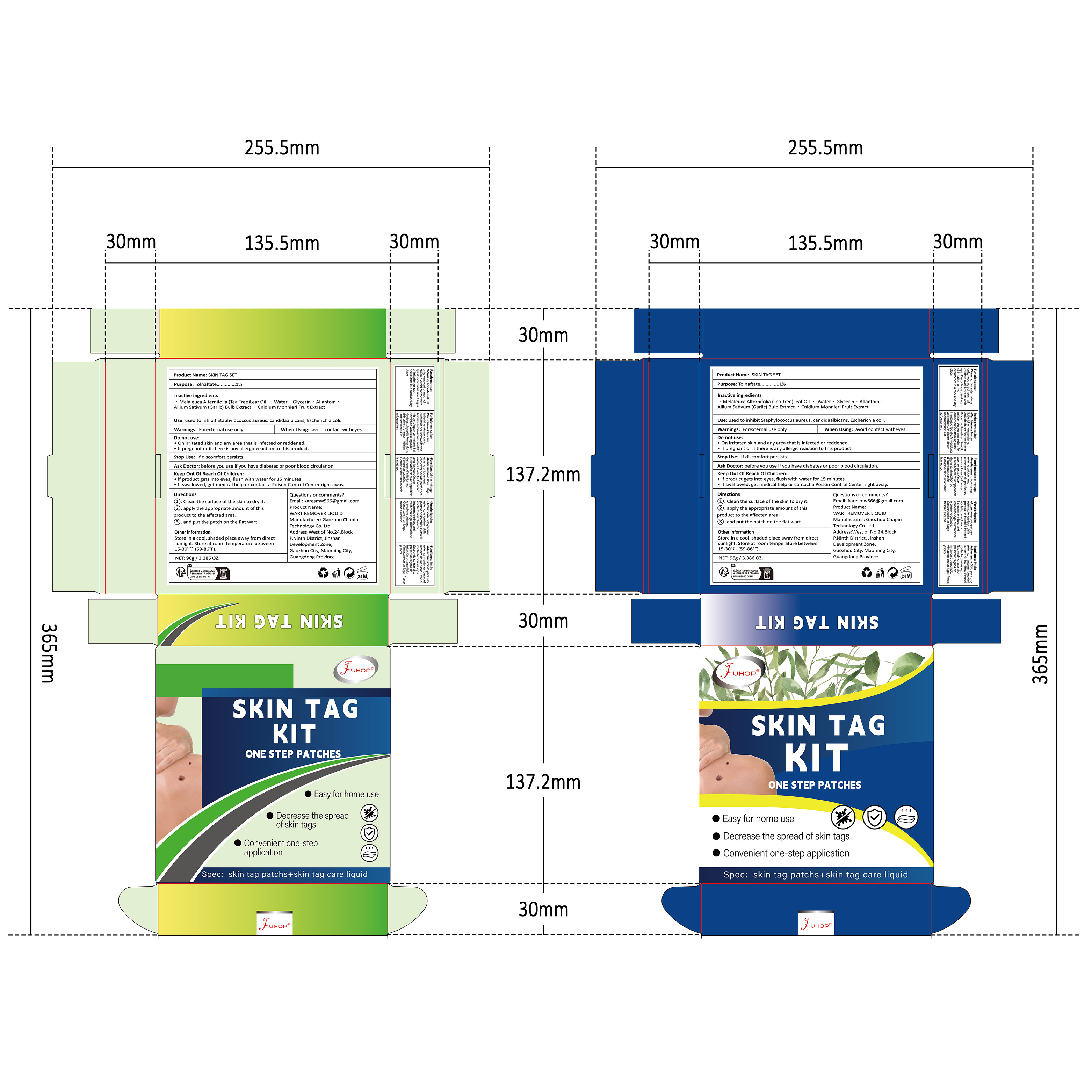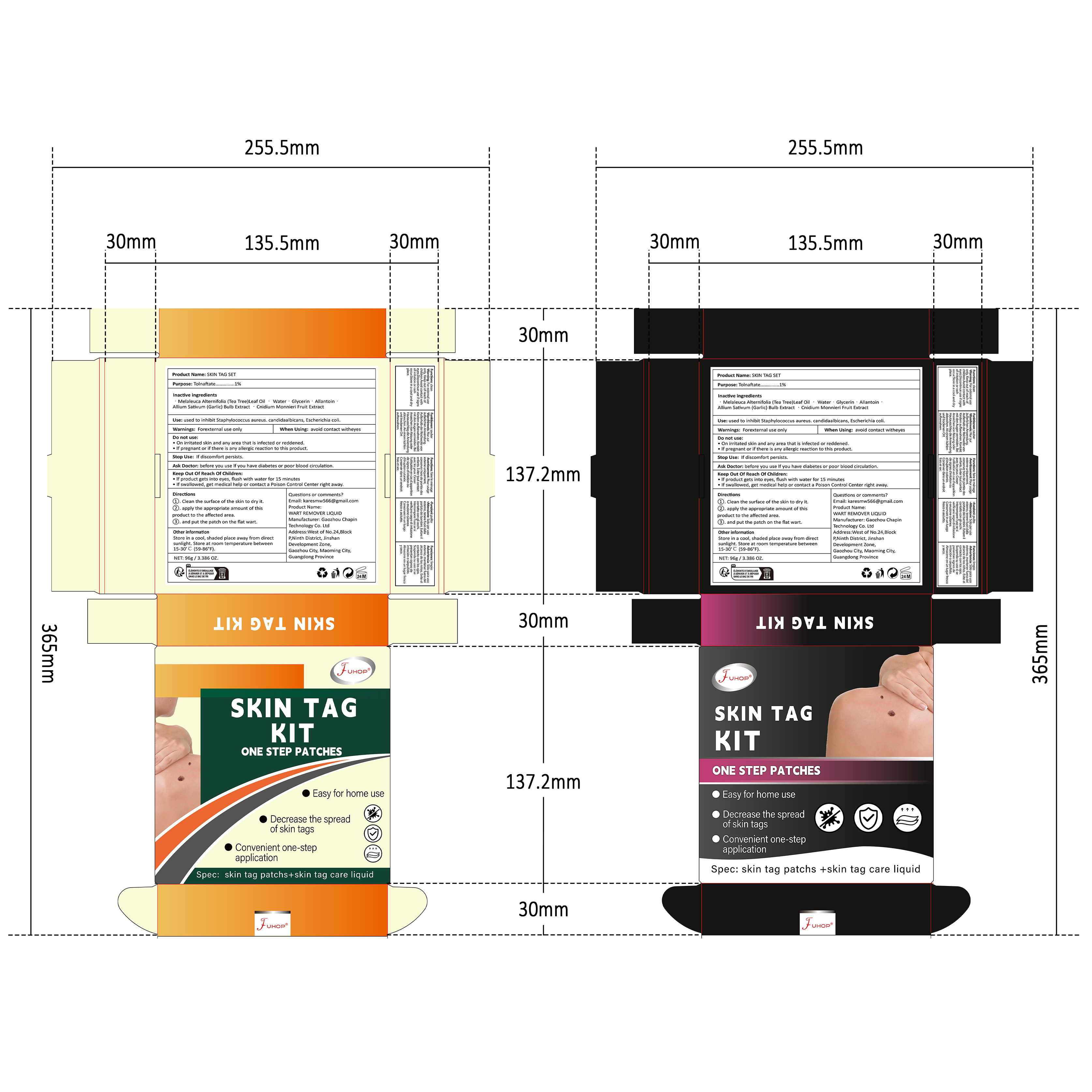 DRUG LABEL: FUHOP SKIN TAG SET
NDC: 84168-048 | Form: LIQUID
Manufacturer: Gaozhou Chapin Technology Co., Ltd
Category: otc | Type: HUMAN OTC DRUG LABEL
Date: 20240926

ACTIVE INGREDIENTS: TOLNAFTATE 1 g/100 g
INACTIVE INGREDIENTS: GARLIC; MELALEUCA ALTERNIFOLIA (TEA TREE) LEAF OIL; WATER; ALLANTOIN; GLYCERIN; CNIDIUM MONNIERI FRUIT

Active ingredients

Tolnaftate 1%

Purpose

Anti-fungal

Use

Proven effective in the treatment of most athlete’s foot (tinea pedis)and ringworm(tinea corporis).

Warnings

For external use only

Do not use

■On irritated skin and any area that is infected or reddened.
■If pregnant or if there is any allergic reaction to this product.

When Using

avoid contact witheyes

Stop Use

If discomfort persists.

Ask Doctor

before you use If you have diabetes or poor blood circulation.

Keep Out Of Reach Of Children

■If product gets into eyes, flush with water for 15 minutes
■If swallowed, get medical help or contact a Poison Control Center right away.

Inactive ingredients

Water,Glycerin, Allantoin, Alum Sativum (Garlic) Bulb Extact, Melaleuca Alternifolia (Tea Tree) Leaf Oil

DOSAGE & ADMINISTRATION SECTION

One patch per day, each patch contains 1 mg of tolnaftate